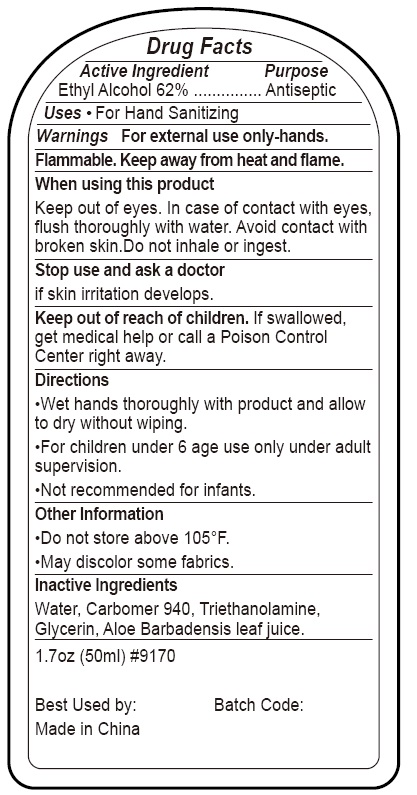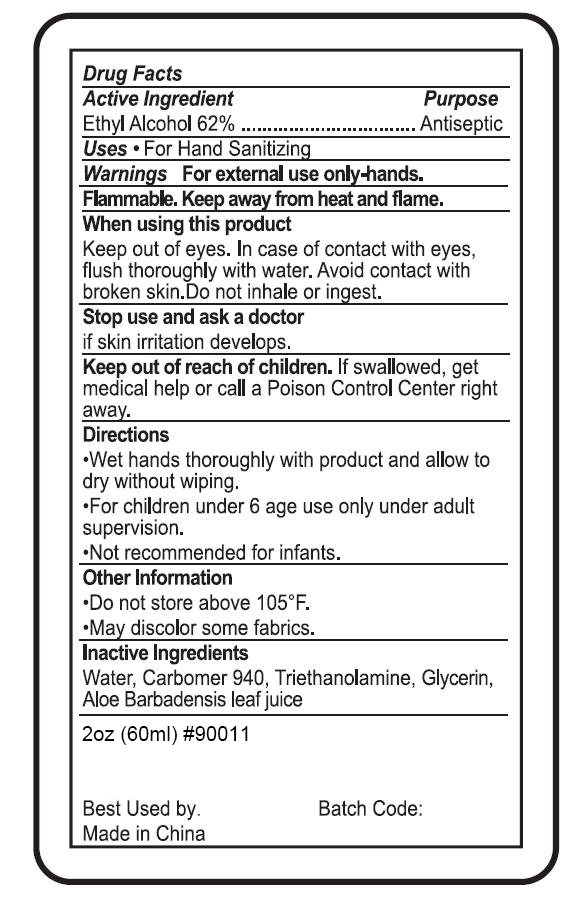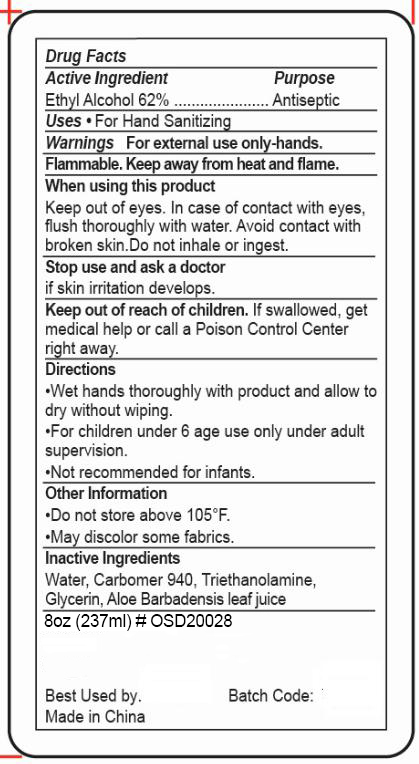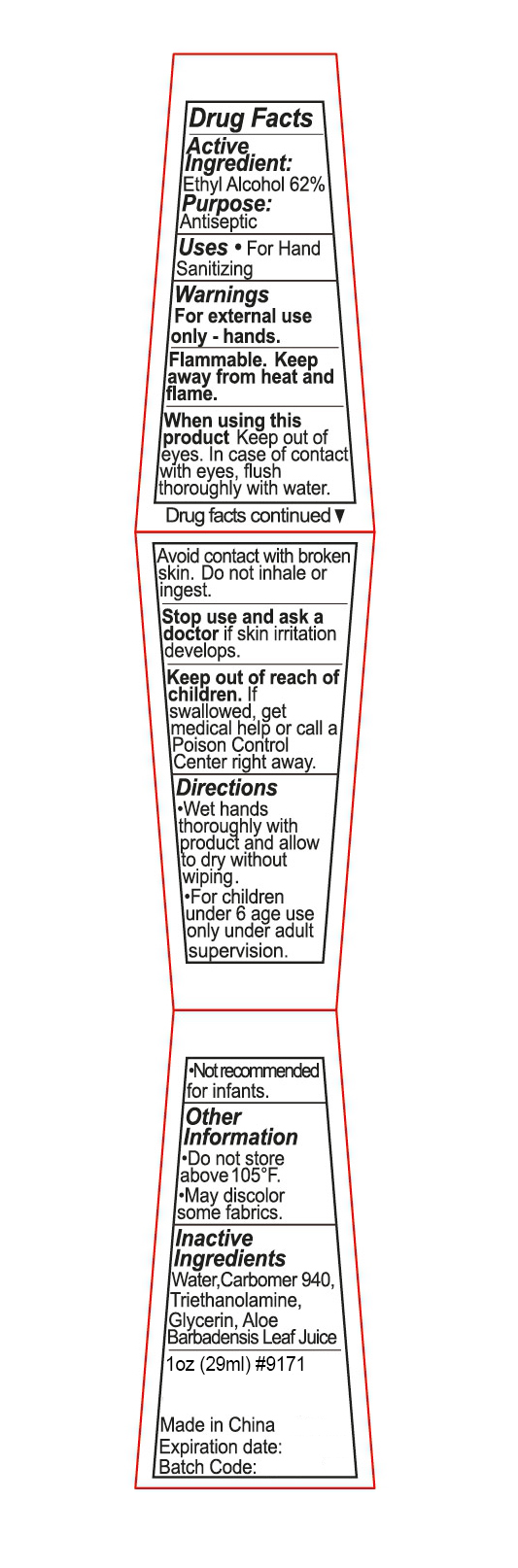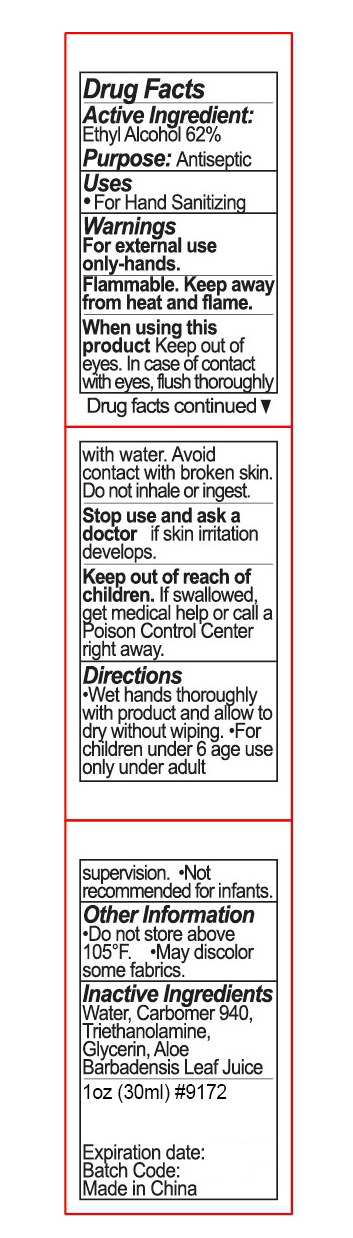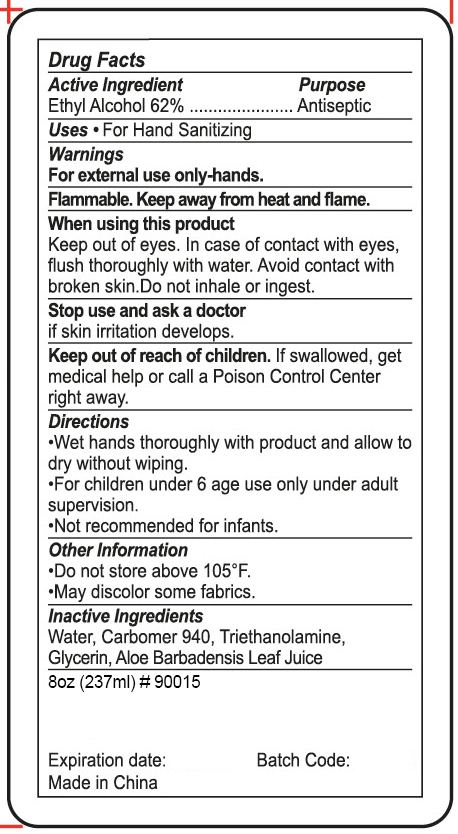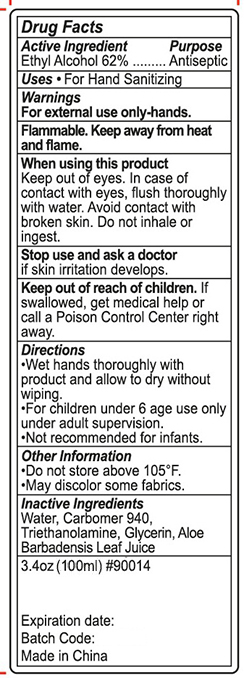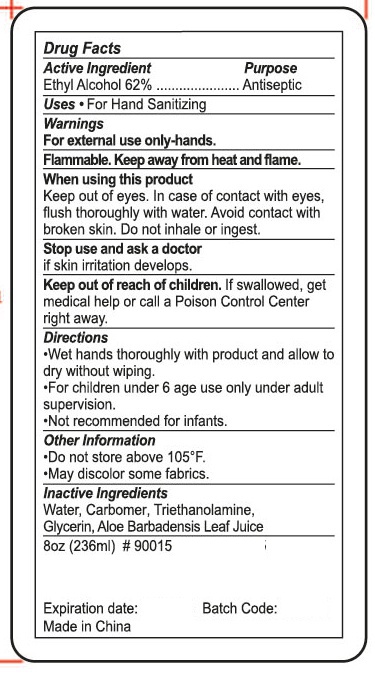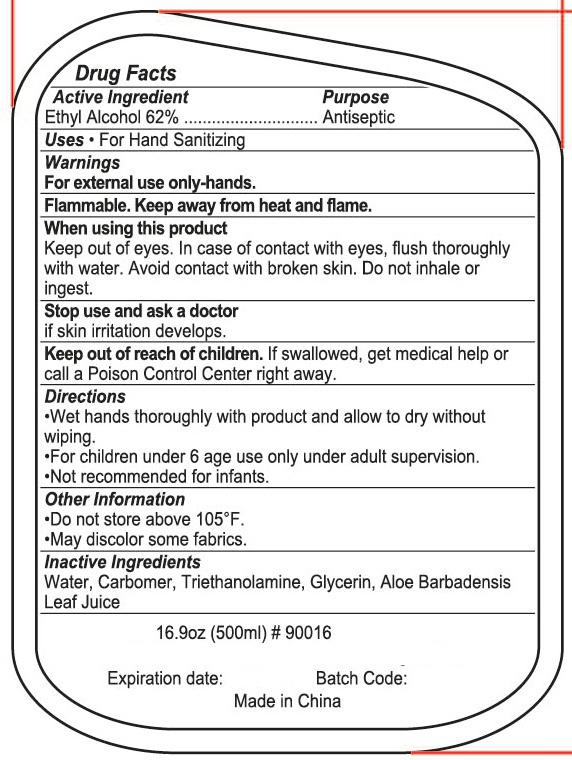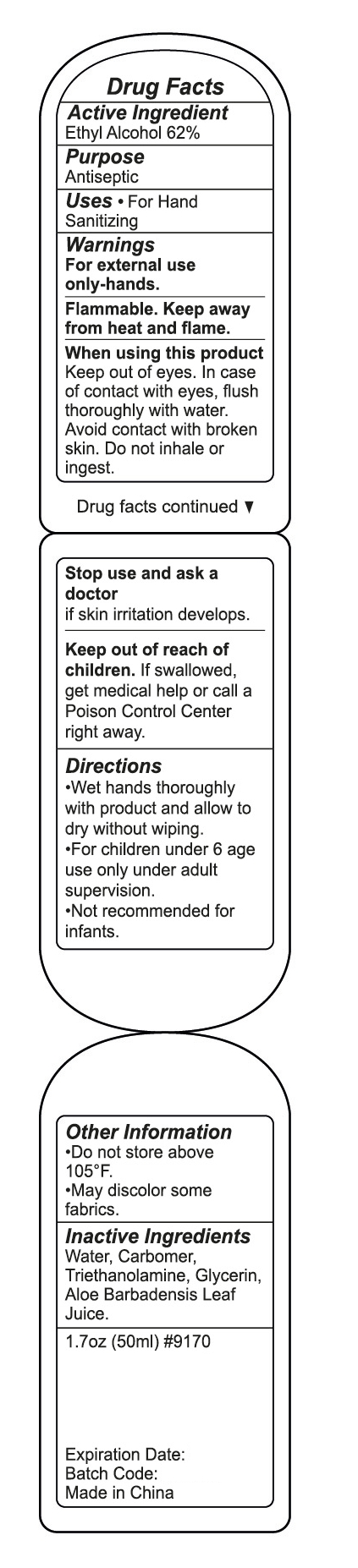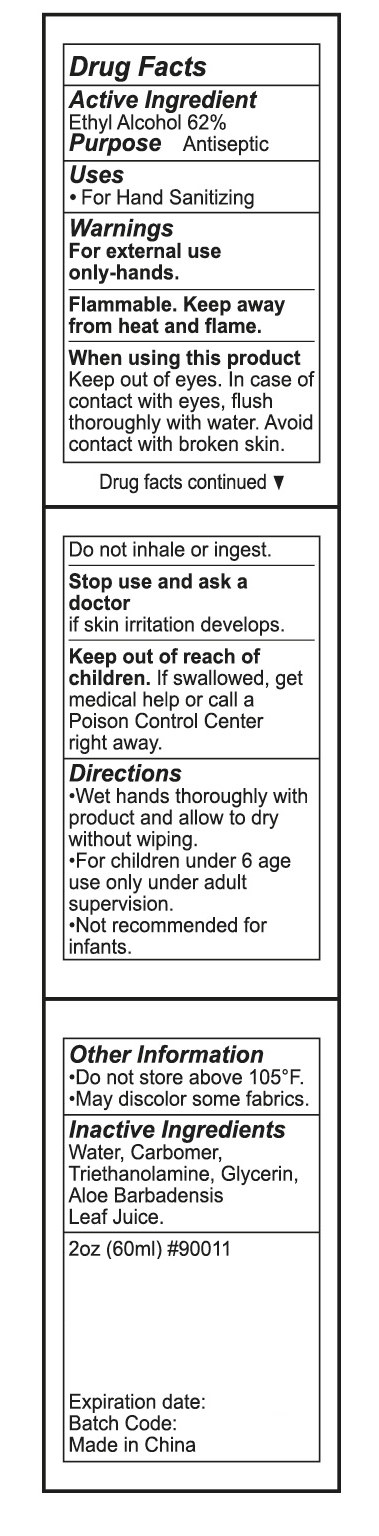 DRUG LABEL: HAND SANITIZER
NDC: 47993-226 | Form: GEL
Manufacturer: NINGBO JIANGBEI OCEAN STAR TRADING CO.,LTD
Category: otc | Type: HUMAN OTC DRUG LABEL
Date: 20201103

ACTIVE INGREDIENTS: ALCOHOL 62 g/112 mL
INACTIVE INGREDIENTS: CARBOMER 940 12 g/112 mL; TRIETHANOLAMINE BENZOATE 3 g/112 mL; ALOE VERA LEAF 1 g/112 mL; WATER 20 g/112 mL; GLYCERIN 2 g/112 mL

47993-226

Active ingredients

Ethyl Alcohol 62%

PURPOSE

Antiseptic

Warnings:

For external use only-hands. Flammable. Keep away from heat and flame.

When using this product

Keep out of eyes. In case of contact with eyes，flush thoroughly with water. Avoid contact with broken skin. Do not inhale or ingest.

Stop use and ask a doctor

If skin Irritation develops.

Keep out of reach of children

If swallowed，get medical help or call a Poison Control Center right away.

Uses：

For hand sanitizing.

Directions:

Wet hands thoroughly with product and allow to dry without wiping.
For children under 6,use only under adult supervision.
Not recommended for infants.

OTHER SAFETY INFORMATION

Do not store above 105℉.
May discolor some fabrics.

Inactive Ingredients:

Water,Carbomer 940,Triethanolamine,Glycerin,Aloe barbadensis leaf juice